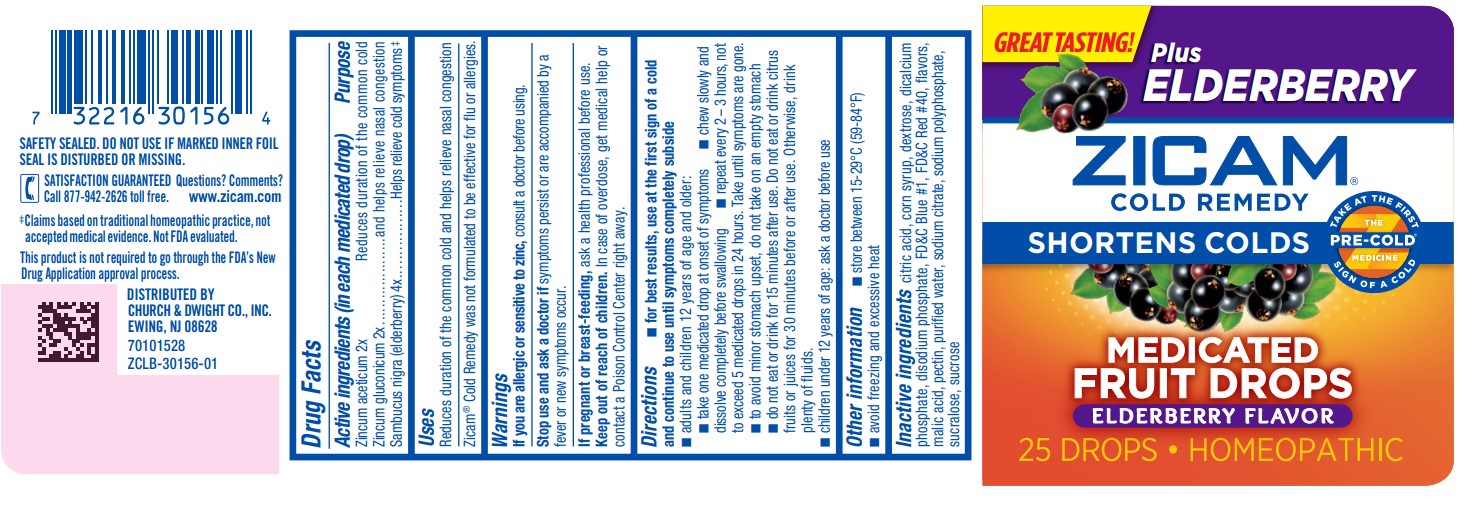 DRUG LABEL: Zicam Cold Remedy Medicated Fruit Drops - Elderberry
NDC: 10237-469 | Form: BAR, CHEWABLE
Manufacturer: Church & Dwight Co., Inc.
Category: homeopathic | Type: HUMAN OTC DRUG LABEL
Date: 20240102

ACTIVE INGREDIENTS: ZINC ACETATE ANHYDROUS 2 [hp_X]/1 1; ZINC GLUCONATE 2 [hp_X]/1 1; SAMBUCUS NIGRA FLOWERING TOP 4 [hp_X]/1 1
INACTIVE INGREDIENTS: CITRIC ACID MONOHYDRATE; CORN SYRUP; DEXTROSE, UNSPECIFIED FORM; ANHYDROUS DIBASIC CALCIUM PHOSPHATE; SODIUM PHOSPHATE, DIBASIC, ANHYDROUS; FD&C BLUE NO. 1; FD&C RED NO. 40; MALIC ACID; PECTIN; WATER; SODIUM CITRATE, UNSPECIFIED FORM; SODIUM POLYMETAPHOSPHATE; SUCRALOSE; SUCROSE

Zicam® Cold Remedy Medicated Fruit Drops - Elderberry

ACTIVE INGREDIENT

Zincum aceticum 2x

Zincum gluconicum 2x

Sambucus nigra (elderberry) 4x

Active ingredients (in each medicated drop) | Purpose
Zincum aceticum 2x Zincum gluconicum 2x | Reduces duration of the common cold and helps relieve nasal congestion
Sambucus nigra (elderberry) 4x | Helps relieve cold symptoms

Uses

Reduces duration of the common cold and helps relieve nasal congestion

Zicam® Cold Remedy was not formulated to be effective for flu or allergies.

Warnings

ASK DOCTOR

If you are allergic or sensitive to zinc, consult a doctor before using.

Stop use and ask a doctor if symptoms persist or are accompanied by a fever or new symptoms occur.

PREGNANCY OR BREAST FEEDING

If pregnant or breast-feeding, ask a health professional before use.

Keep out of reach of children. In case of overdose, get medical help or contact a Poison Control Center right away.

Directions

- for best results, use at the first sign of a cold and continue to use until symptoms completely subside
- adults and children 12 years of age and older:
  - take one medicated drop at onset of symptoms
  - chew slowly and dissolve completely before swallowing
  - repeat every 2 – 3 hours, not to exceed 5 medicated drops in 24 hours. Take until symptoms are gone.
  - to avoid minor stomach upset, do not take on an empty stomach
  - do not eat or drink for 15 minutes after use. Do not eat or drink citrus fruits or juices for 30 minutes before or after use. Otherwise, drink plenty of fluids.
- children under 12 years of age: ask a doctor before use

Other information

- store between 15-29°C (59-84°F)
- avoid freezing and excessive heat

Inactive ingredients

citric acid, corn syrup, dextrose, dicalcium phosphate, disodium phosphate, FD&C Blue #1, FD&C Red #40, flavors, malic acid, pectin, purified water, sodium citrate, sodium polyphosphate, sucralose, sucrose

PRINCIPAL DISPLAY PANEL - 25 Drop Bottle Label

GREAT TASTING!

Plus
ELDERBERRY

ZICAM®
COLD REMEDY

SHORTENS COLDS

TAKE AT THE FIRST
SIGN OF A COLD

THE
PRE-COLD®
MEDICINE

MEDICATED
FRUIT DROPS

ELDERBERRY FLAVOR

25 DROPS • HOMEOPATHIC